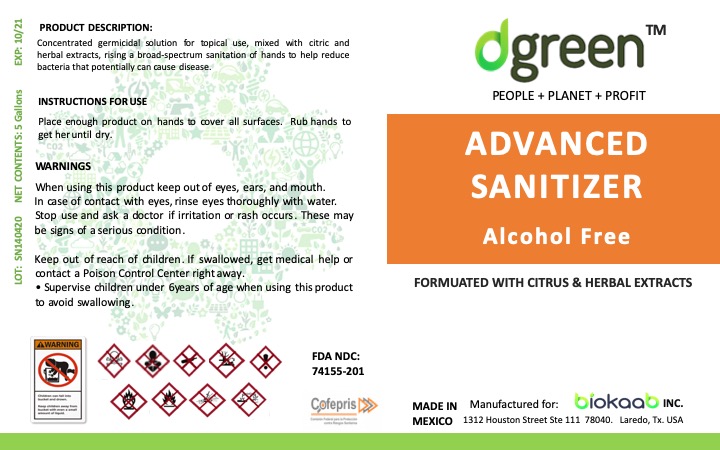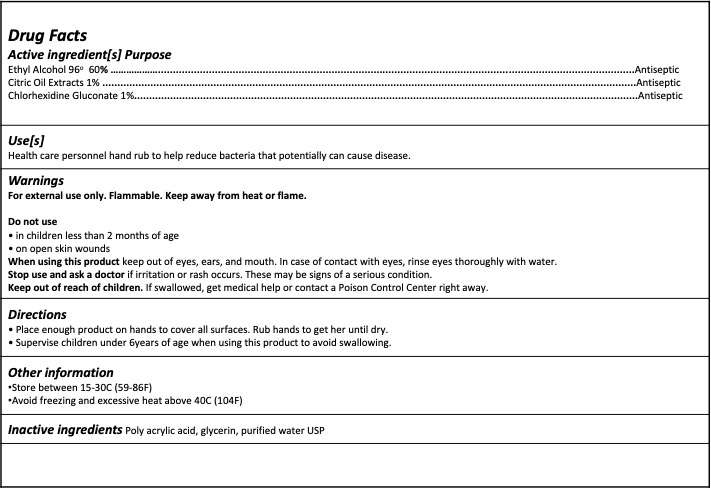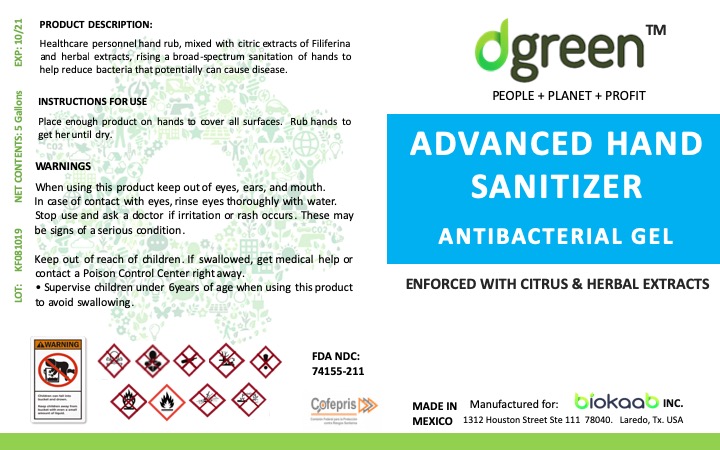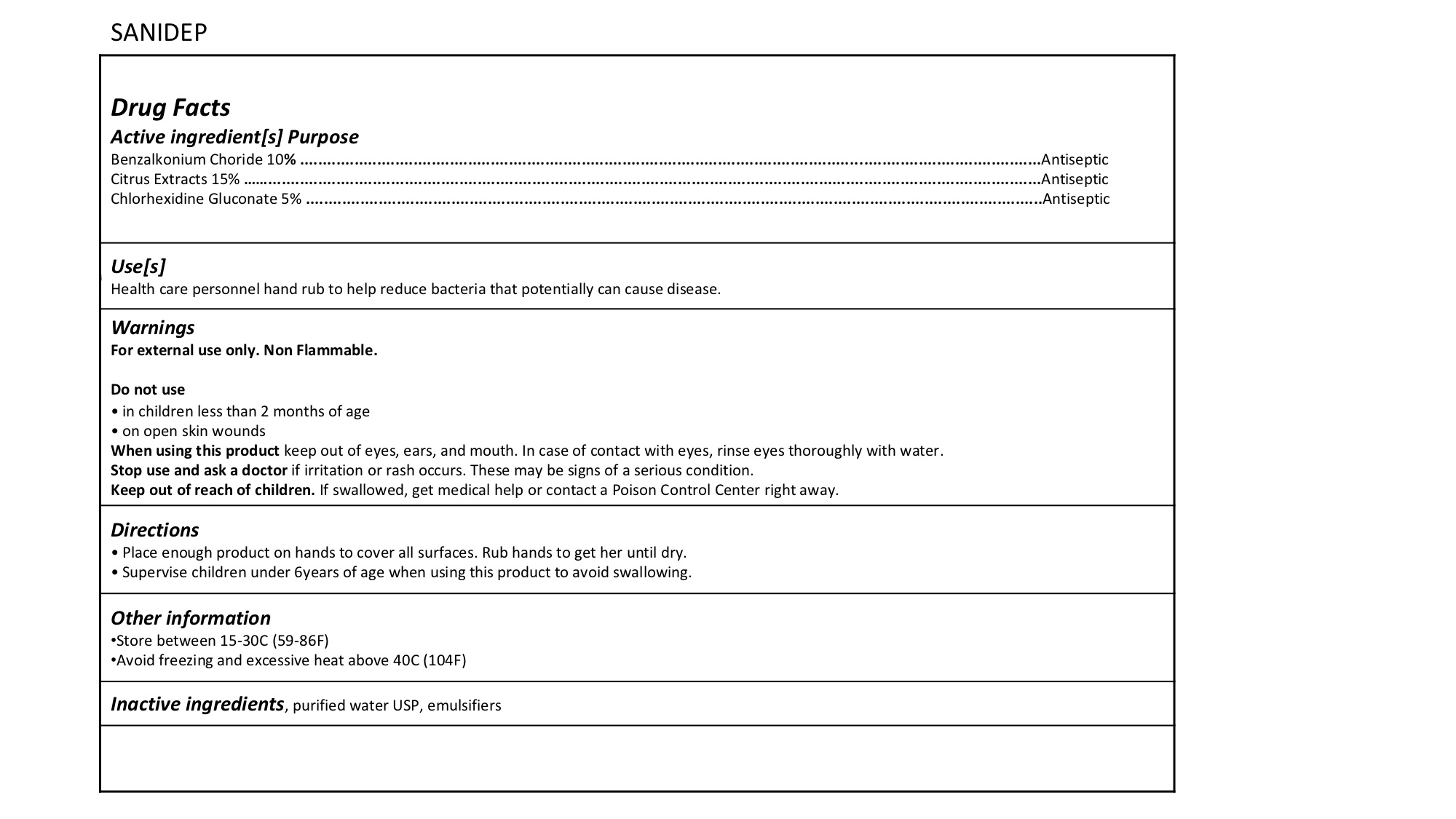 DRUG LABEL: Hand Sanitizer Gel
NDC: 74155-101 | Form: GEL
Manufacturer: Biokaab Inc
Category: otc | Type: HUMAN OTC DRUG LABEL
Date: 20200520

ACTIVE INGREDIENTS: ALCOHOL 600 mg/1 mL; GRAPEFRUIT OIL 10 mg/1 mL; CHLORHEXIDINE GLUCONATE 10 mg/1 mL
INACTIVE INGREDIENTS: WATER 375 mg/1 mL; GLYCERIN 5 mg/1 mL; POLYACRYLIC ACID (250000 MW) 6 mg/1 mL

NDC 74155-202 DEQGEL ADVANCED HAND SANITIZER GEL LABEL

HAND SANITIZER GEL LABEL

DEQGEL Hand Sanitizer Gel Active Ingredients

Active ingredient[s] Purpose

- Ethyl Alcohol 96o 60%......................................................................................................................................................Antiseptic
- Citric Oil Extracts 1%.........................................................................................................................................................Antiseptic
- Chlorhexidine Gluconate 1%.............................................................................................................................................Antiseptic

DEQGEL Dossage and Administration

Place enough product on hands to cover all surfaces. Rub hands to get her until dry.

Indications

Place enough product on hands to cover all surfaces. Rub hands to get her until dry.

Hand Sanitizer Gel Warnings

Warnings

For external use only. Flammable. Keep away from heat or flame.

Do not use
• in children less than 2 months of age
• on open skin wounds

When using this product keep out of eyes, ears, and mouth. In case of contact with eyes, rinse eyes thoroughly with water.

Stop use and ask a doctor if irritation or rash occurs. These may be signs of a serious condition.
Keep out of reach of children. If swallowed, get medical help or contact a Poison Control Center right away.

Inactive Ingedients

Inactive ingredients, Poly acrylic acid, glycerin, purified water USP

HandSanitizerGel

Keep out of reach of children. If swallowed, get medical help or contact a Poison Control Center right away.

Purpose

Health care personnel hand rub to help reduce bacteria that potentially can cause disease.

Active ingredient[s] Purpose

Ethyl Alcohol 96o 60% ……………….....................................................................................................................................Antiseptic

Citric Oil Extracts 1% ..............................................................................................................................................................Antiseptic

Chlorhexidine Gluconate 1%...................................................................................................................................................Antiseptic

NDC 74155-211 SANIDEP Alcohol Free Hand Sanitizer

SANIDEP ALCOHOL FREE HAND SANITIZER

For external use only. NON Flammable.

Do not use

• in children less than 2 months of age
• on open skin wounds
When using this product keep out of eyes, ears, and mouth. In case of contact with eyes, rinse eyes thoroughly with water. Stop use and ask a doctor if irritation or rash occurs. These may be signs of a serious condition.

SANIDEP Active Ingredients

Benzalkonium Choride 10% ........................................................................................................................................................Antiseptic

Citric Extracts 15% ......................................................................................................................................................................Antiseptic

Chlorhexidine Gluconate 5% .......................................................................................................................................................Antiseptic

INSTRUCTIONS SANIDEP

Place enough product on hands to cover all surfaces. Rub hands to get her until dry.

KEEP OUT OF CHILDREN

Keep out of reach of children. If swallowed, get medical help or contact a Poison Control Center right away.

Supervise children under 6years of age when using this product to avoid swallowing.

Inactive Ingredients

Purified water USP, emulsifiers

Purpose

Active ingredient[s] Purpose

Benzalkonium Choride 10% ........................................................................................................................................................Antiseptic

Citric Extracts 15% ......................................................................................................................................................................Antiseptic

Chlorhexidine Gluconate 5% .......................................................................................................................................................Antiseptic

Use[s]

Health care personnel hand rub to help reduce bacteria that potentially can cause disease.